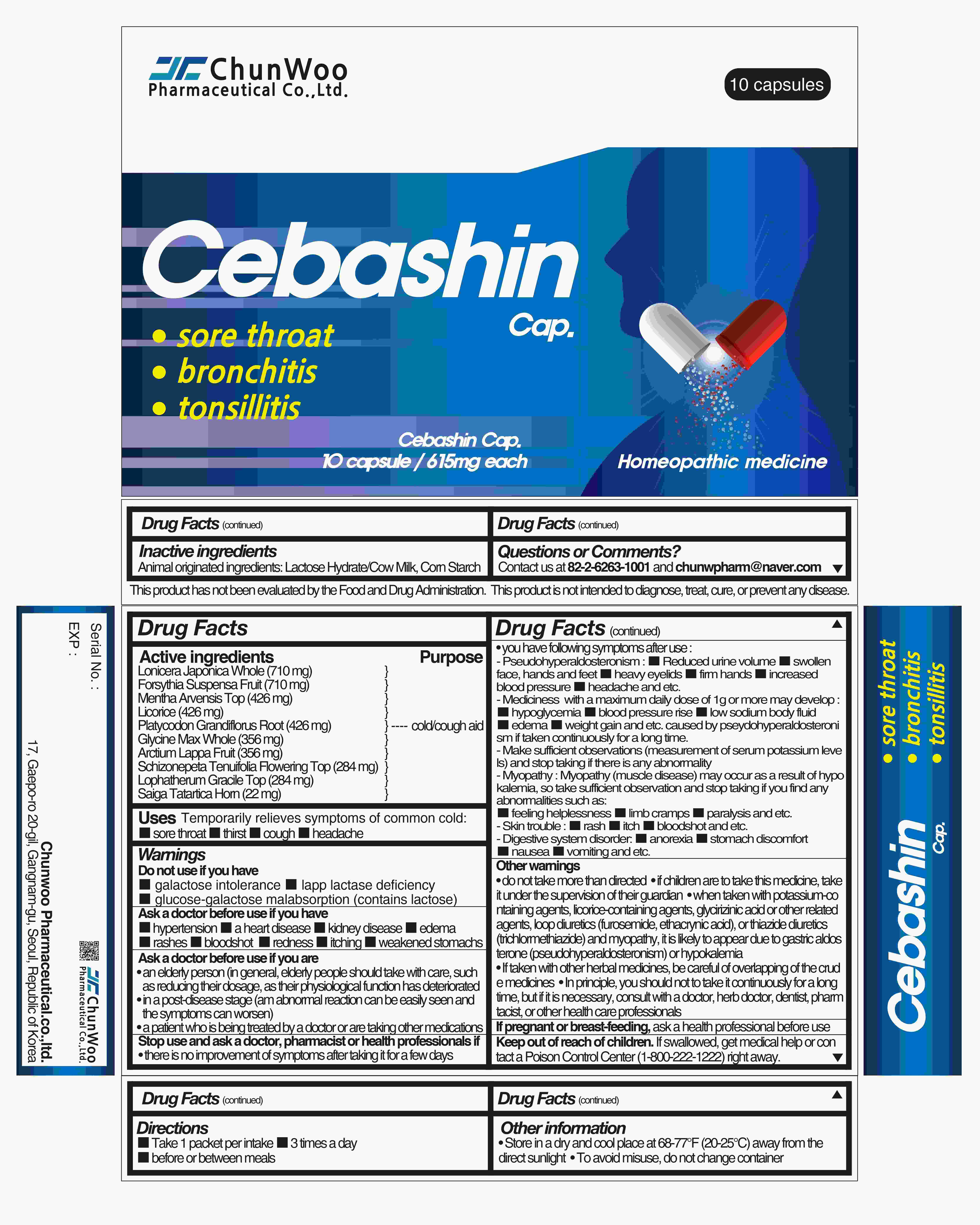 DRUG LABEL: Cebashin Cap.
NDC: 72850-0007 | Form: CAPSULE
Manufacturer: Chunwoo Pharmaceutical Co., Ltd.
Category: homeopathic | Type: HUMAN OTC DRUG LABEL
Date: 20220131

ACTIVE INGREDIENTS: FORSYTHIA SUSPENSA FRUIT 710 mg/10 g; LICORICE 426 mg/10 g; PLATYCODON GRANDIFLORUS ROOT 426 mg/10 g; ARCTIUM LAPPA FRUIT 356 mg/10 g; LONICERA JAPONICA WHOLE 710 mg/10 g; MENTHA ARVENSIS TOP 426 mg/10 g; GLYCINE MAX WHOLE 356 mg/10 g; SCHIZONEPETA TENUFOLIA SPIKE 284 mg/10 g; LOPHATHERUM GRACILE TOP 284 mg/10 g; SAIGA TATARICA HORN 22 mg/10 g
INACTIVE INGREDIENTS: LACTOSE MONOHYDRATE

Cebashin Cap.

Active ingredients

FORSYTHIA SUSPENSA FRUIT }

LONICERA JAPONICA WHOLE }

MENTHA ARVENSIS TOP }

PLATYCODON GRANDIFLORUS ROOT }

LICORICE }

ARCTIUM LAPPA FRUIT } ----------------------------------------- cold / cough aid

GLYCINE MAX WHOLE }

LOPHATHERUM GRACILE TOP }

SCHIZONEPETA TENUFOLIA SPIKE }

SAIGA TATARICA HORN }

Purpose

Cold/cough aid

Directions

For adults, take 1 packet per intake, 3 times a day, before or between meals

Inactive ingredients

Corn Starch, Animal originated ingredients: Lactose Hydrate/Cow Milk

Keep out of reach of children. If swallowed, get medical help or contact a Poison Control Center (1-800-222-1222) right away.

Warnings

Do not use if you are

- Children under 5 years old

Do not use if you have

- Galactose intolerance
- Lapp lactase deficiency
- Glucose-galactose malabsorption (this medicine contains lactose)

Ask a doctor before use if you

- have hypertension
- have a heart disease or a kidney disease
- a patient with edema
- pregnant or have a chance to pregnant
- a patient who has rashes, bloodshot, redness, itching, and etc. caused by medication
- a patient with significantly weakened stomachs
- an elderly person (in general, elderly people should take with care, such as reducing their dosage, as their physiological function has deteriorated)
- in a post-disease stage (am abnormal reaction can be easily seen and the symptoms can worsen)
- a patient who is being treated by a doctor or are taking other medications

Stop use and ask a doctor, pharmacist or health professionals if

- if there is no improvement in symptoms after taking it for a few days
- you have following symptoms after use:

- Pseudohyperaldosteronism: Reduced urine volume, swollen face, swollen hands and feet, heavy eyelids, firm hands, increased blood pressure, headache, and etc. (Mediciness with a maximum daily dose of 1g or more may develop hypoglycemia, blood pressure rise, low sodium body fluid, edema, weight gain, and etc. caused by pseydohyperaldosteronism if taken continuously for a long time. Therefore, make sufficient observations (measurement of serum potassium levels) and stop taking if there is any abnormality.)

-Myopathy: Myopathy (muscle disease) may occur as a result of hypokalemia, so take sufficient observation and stop taking if you find any abnormalities such as feeling helplessness, limb cramps, paralysis, and etc.

-Skin trouble: a rash, itch, bloodshot, and etc.

-Digestive system disorder: anorexia, stomach discomfort, nausea, vomiting, and etc.

Other Warnings

- do not take more than directed
- if children are to take this medicine, take it under the supervision of their guardian.
- when taken with potassium-containing agents, licorice-containing agents, glycirizinic acid or other related agents, loop diuretics (furosemide, ethacrynic acid), or thiazide diuretics (trichlormethiazide) and myopathy, it is likely to appear due to gastric aldosterone (pseudohyperaldosteronism) or hypokalemia
- If taken with other herbal medicines, be careful of overlapping of the crude medicines.
- In principle, you should not to take it continuously for a long time, but if it is necessary, consult with a doctor, herb doctor, dentist, pharmacist, or other health care professionals.

Uses

a sore throat, thirst, cough, headache from a cold